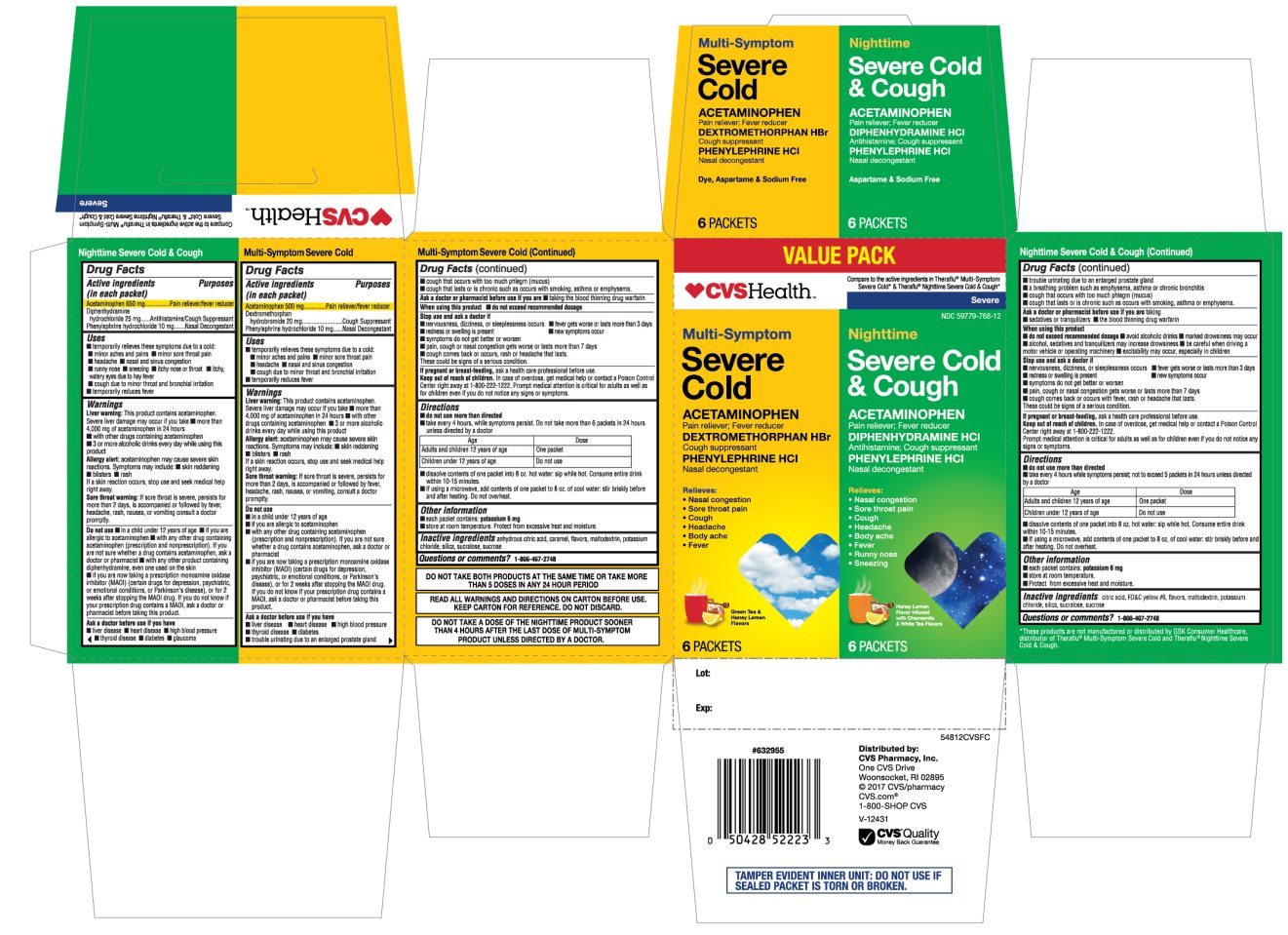 DRUG LABEL: Multi Symptom Severe Cold and Nighttime Severe Cold and Cough
NDC: 59779-768 | Form: KIT | Route: ORAL
Manufacturer: CVS Pharmacy,Inc.
Category: otc | Type: HUMAN OTC DRUG LABEL
Date: 20251208

ACTIVE INGREDIENTS: ACETAMINOPHEN 500 mg/1 1; DEXTROMETHORPHAN HYDROBROMIDE 20 mg/1 1; PHENYLEPHRINE HYDROCHLORIDE 10 mg/1 1; ACETAMINOPHEN 650 mg/1 1; DIPHENHYDRAMINE HYDROCHLORIDE 25 mg/1 1; PHENYLEPHRINE HYDROCHLORIDE 10 mg/1 1
INACTIVE INGREDIENTS: ANHYDROUS CITRIC ACID; CARAMEL; MALTODEXTRIN; POTASSIUM CITRATE; SILICON DIOXIDE; SUCRALOSE; SUCROSE; ANHYDROUS CITRIC ACID; FD&C YELLOW NO. 6; MALTODEXTRIN; POTASSIUM CHLORIDE; SILICON DIOXIDE; SUCRALOSE; SUCROSE

CVS Health Multi Symptom Severe Cold and Nighttime Severe Cold and Cough Value Pack

Active ingredients (in each packet) – Multi Symptom Severe Cold

Acetaminophen 500 mg

Dextromethorphan hydrobromide 20 mg

Phenylephrine hydrochloride 10 mg

Active ingredients (in each packet) - Nighttime Severe Cold and Cough

Acetaminophen 650 mg

Diphenhydramine hydrochloride 25 mg

Phenylephrine hydrochloride 10 mg

Purpose - Multi Symptom Severe Cold

Pain reliever/fever reducer

Cough Suppressant

Nasal Decongestant

Purpose - Nighttime Severe Cold and Cough

Pain reliever/fever reducer

Antihistamine/cough suppressant

Nasal decongestant

Uses - Multi Symptom Severe Cold

- temporarily relieves these symptoms due to a cold:
- minor aches and pains
- minor sore throat pain
- headache
- nasal and sinus congestion
- cough due to minor throat and bronchial irritation
- temporarily reduces fever

Uses - Nighttime Severe Cold and Cough

- temporarily relieves these symptoms due to a cold:
- minor aches and pains
- minor sore throat pain
- headache
- nasal and sinus congestion
- runny nose
- sneezing
- itchy nose or throat
- itchy, watery eyes due to hay fever
- cough due to minor throat and bronchial irritation
- temporarily reduces fever

Warnings – Multi Symptom Severe Cold /Nighttime Severe Cold and Cough

Liver warning: This product contains acetaminophen. Severe liver damage may occur if you take

- more than 4,000 mg of acetaminophen in 24 hours
- with other drugs containing acetaminophen
- 3 or more alcoholic drinks every day while using this product

Sore throat warning: If sore throat is severe, persists for more than 2 days, is accompanied or followed by fever, headache, rash, nausea, or vomiting, consult a doctor promptly.

Do not use - Multi Symptom Severe Cold

- in a child under 12 years of age
- if you are allergic to acetaminophen
- with any other drug containing acetaminophen (prescription or nonprescription). If you are not sure whether a drug contains acetaminophen, ask a doctor or a pharmacist.
- if you are now taking a prescription monoamine oxidase inhibitor (MAOI) (certain drugs for depression, psychiatric, or emotional conditions, or Parkinson's disease), or for 2 weeks after stopping the MAOI drug. If you do not know if your prescription drug contains an MAOI, ask a doctor or pharmacist before taking this product.

Do not use - Nighttime Severe Cold and Cough

- in a child under 12 years of age
- if you are allergic to acetaminophen
- with any other drug containing acetaminophen (prescription or nonprescription). If you are not sure whether a drug contains acetaminophen, ask a doctor or a pharmacist.
- with any other product containing diphenhydramine, even one used on skin
- if you are now taking a prescription monoamine oxidase inhibitor (MAOI) (certain drugs for depression, psychiatric, or emotional conditions, or Parkinson’s disease), or for 2 weeks after stopping the MAOI drug. If you do not know if your prescription drug contains an MAOI, ask a doctor or pharmacist before taking this product.

Ask a doctor before use if you have - Multi Symptom Severe Cold

- liver disease
- heart disease
- high blood pressure
- thyroid disease
- diabetes
- trouble urinating due to an enlarged prostate gland
- cough that occurs with too much phlegm (mucus)
- cough that lasts or is chronic such as occurs with smoking, asthma, or emphysema

Ask a doctor before use if you have - Nighttime Severe Cold and Cough

- liver disease
- heart disease
- high blood pressure
- thyroid disease
- diabetes
- glaucoma
- a sodium restricted diet
- trouble urinating due to an enlarged prostate gland
- a breathing problem such as emphysema or chronic bronchitis
- cough that occurs with too much phlegm (mucus)
- cough that lasts or is chronic such as occurs with smoking, asthma, or emphysema

Ask a doctor or pharmacist before use if you are - Multi Symptom Severe Cold

taking the blood thinning drug warfarin

Ask a doctor or pharmacist before use if you are - Nighttime Severe Cold and Cough

- taking sedatives or tranquilizers
- taking the blood thinning drug warfarin

When using this product - Multi Symptom Severe Cold

do not exceed recommended dosage

When using this product - Nighttime Severe Cold and Cough

- do not exceed recommended dosage
- avoid alcoholic drinks
- marked drowsiness may occur
- alcohol, sedatives, and tranquilizers may increase drowsiness
- be careful when driving a motor vehicle or operating machinery
- excitability may occur, especially in children

Stop use and ask a doctor if – Multi Symptom Severe Cold /Nighttime Severe Cold and Cough

- nervousness, dizziness, or sleeplessness occurs
- fever gets worse or lasts more than 3 days
- redness or swelling is present
- new symptoms occur
- symptoms do not get better or worsen
- pain, cough or nasal congestion gets worse or lasts more than 7 days
- cough comes back or occurs with fever, rash or headache that lasts. These could be signs of a serious condition.

If pregnant or breast-feeding,

ask a health professional before use.

Keep out of reach of children.

Overdose warning: In case of overdose, get medical help or contact a Poison Control Center right away (1-800-222-1222). Prompt medical attention is critical for adults as well as for children even if you do not notice any signs or symptoms.

Directions – Multi Symptom Severe Cold

- do not use more than directed
- take every 4 hours, while symptoms persist; Do not to take 6 packets in 24 hours or as directed by a doctor

1. Age

1. Dose

1. Adults and children 12 years of age

1. One packet

1. Children under 12 years of age

1. Do not use

Directions Nighttime Severe Cold and Cough

- do not use more than directed
- take every 4 hours while symptoms persist;; not to exceed 5 packets in 24 hours or as directed by a doctor

1. Age

1. Dose

1. Adults and children 12 years of age

1. One packet

1. Children under 12 years of age

1. Do not use

- Dissolve contents of one packet into 8 oz. hot water: sip while hot. Consume entire drink within 10-15 minutes
- If using a microwave, add contents of one packet to 8 oz. of cool water: stir briskly before and after heating. Do not overheat.

Other information - Multi Symptom Severe Cold

- each packet contains: potassium 6 mg
- store at controlled room temperature. Protect from excessive heat and moisture.

Other information - Nighttime Severe Cold and Cough

- each packet contains: potassium 6 mg
- store at room temperature. Protect from excessive heat and moisture.

Inactive ingredients - Multi Symptom Severe Cold

anhydrous citric acid, caramel, flavors, maltodextrin, potassium citrate, silica, sucralose, sucrose

Inactive ingredients - Nighttime Severe Cold and Cough

citric acid, FD&C yellow #6, flavors, maltodextrin, potassium chloride, silica ,sucralose, sucrose.

Questions or comments?

1-866-467-2748

Package/Label Principal Display Panel

Multi Symptom Severe Cold 6 PACKETS + NIGHTTIME 6 PACKETS = 12 PACKETS TOTAL

Compare to the active ingredients in Theraflu® Multi Symptom Severe Cold* & Theraflu®Nighttime Severe Cold & Cough*

Multi Symptom

Severe Cold

ACETAMINOPHEN - Pain reliever; Fever reducer

DEXTROMETHORPHAN HBr – Cough suppressant

PHENYLEPHRINE HCl – Nasal decongestant

Relieves:

- Nasal congestion
- Sore throat pain
- Cough
- Headache
- Body ache
- Fever

Green Tea & Honey Lemon Flavors

6 PACKETS

NIGHTTIME

Severe Cold & Cough

ACETAMINOPHEN - Pain reliever; Fever reducer

DIPHENHYDRAMINE HCl – Antihistamine; Cough suppressant

PHENYLEPHRINE HCl – Nasal decongestant

Relieves:

- Nasal congestion
- Sore throat pain
- Cough
- Headache
- Body ache
- Fever
- Runny nose
- Sneezing

Honey Lemon Flavor Infused with Chamomile &White Tea Flavors

6 PACKETS

Distributed by:

CVS Pharmacy, Inc.

One CVS Drive

Woonsocket, RI 02895

© 2017 CVS/pharmacy

CVS.com®

1-800-SHOP CVS

Money Back Guarantee

*These products are not manufactured or distributed by GSK Consumer Healthcare, distributor of Theraflu®Multi-Symptom Severe Cold and Theraflu®Nighttime Severe Cold & Cough.